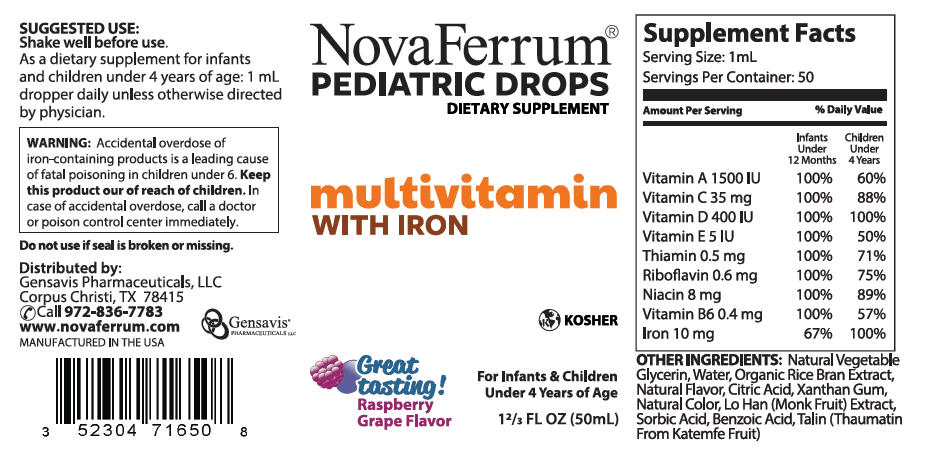 DRUG LABEL: NovaFerrum 
NDC: 52304-716 | Form: LIQUID
Manufacturer: Gensavis Pharmaceuticals, LLC
Category: other | Type: DIETARY SUPPLEMENT
Date: 20190814

ACTIVE INGREDIENTS: Iron 10 mg/1 mL; Vitamin A 1500 [iU]/1 mL; Ascorbic Acid 35 mg/1 mL; Vitamin D 400 [iU]/1 mL; .Alpha.-Tocopherol 5 [iU]/1 mL; Thiamine 0.5 mg/1 mL; Riboflavin 0.6 mg/1 mL; Niacin 8 mg/1 mL; Pyridoxine 0.4 mg/1 mL
INACTIVE INGREDIENTS: Water; Citric Acid Monohydrate; Xanthan Gum; Siraitia Grosvenorii Fruit; Sorbic Acid; Benzoic Acid

NovaFerrum®
PEDIATRIC DROPS
DIETARY SUPPLEMENT

STATEMENT OF IDENTITY

Supplement Facts
Serving Size: 1 mL Servings Per Container: 50
Amount Per Serving | % Daily Value
 | Infants Under 12 Months | Children Under 4 Years
Vitamin A 1500 IU | 100% | 60%
Vitamin C 35 mg | 100% | 88%
Vitamin D 400 IU | 100% | 100%
Vitamin E 5 IU | 100% | 50%
Thiamin 0.5 mg | 100% | 71%
Riboflavin 0.6 mg | 100% | 75%
Niacin 8 mg | 100% | 89%
Vitamin B6 0.4 mg | 100% | 57%
Iron 10 mg | 67% | 100%

OTHER INGREDIENTS: Natural Vegetable Glycerin, Water, Organic Rice Bran Extract, Natural Flavor, Citric Acid, Xanthan Gum, Natural Color, Lo Han (Monk Fruit) Extract, Sorbic Acid, Benzoic Acid, Talin (Thaumatin From Katemfe Fruit)

SUGGESTED USE

Shake well before use.

As a dietary supplement for infants and children under 4 years of age: 1 mL dropper daily unless otherwise directed by physician.

WARNINGS

WARNING: Accidental overdose of iron-containing products is a leading cause of fatal poisoning in children under 6. Keep this product our of reach of children. In case of accidental overdose, call a doctor or poison control center immediately.

Do not use if seal is broken or missing.

STATEMENT OF IDENTITY

Distributed by:
Gensavis Pharmaceuticals, LLC
Corpus Christi, TX 78415
Call 972-836-7783
www.novaferrum.com
MANUFACTURED IN THE USA

PRINCIPAL DISPLAY PANEL - 50 mL Bottle Label

NovaFerrum®
PEDIATRIC DROPS
DIETARY SUPPLEMENT

multivitamin
WITH IRON

KOSHER

Great
tasting!
Raspberry
Grape Flavor

For Infants & Children
Under 4 Years of Age

1⅔ FL OZ (50mL)